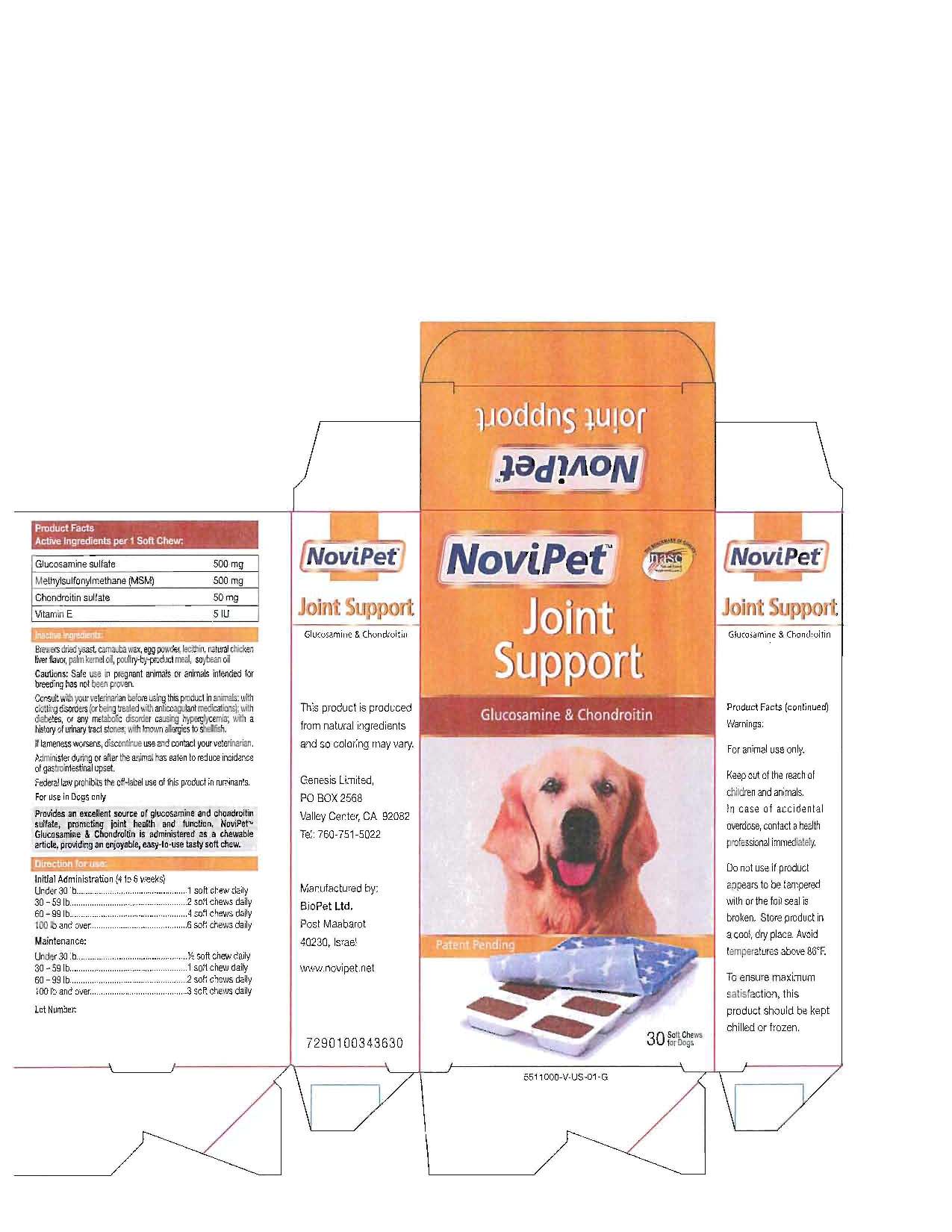 DRUG LABEL: Novipet
NDC: 16244-1004 | Form: TABLET, CHEWABLE
Manufacturer: LDSE International LLC
Category: animal | Type: OTC ANIMAL DRUG LABEL
Date: 20111018

ACTIVE INGREDIENTS: GLUCOSAMINE SULFATE 500 mg/1 1; CHONDROITIN SULFATE SODIUM (BOVINE) 50 mg/1 1; DIMETHYL SULFONE 500 mg/1 1; TOCOPHEROL 5 mg/1 1

NOVIPET JOINT SUPPORT

FRONT PANEL

NoviPet
Joint
Support
Glucosamine and Chondroitin
30 Soft Chews for Dogs

SIDE PANELS

Carton left side panel

NoviPet
Joint Support
Glucosamine and Chondrotin
This product is produced from natural ingredients and so coloring may vary.
Genesis Limited
PO Box 2568
Valley Center, CA 92082
Tel. 760-751-5022
Manufactured by:
BioPet Ltd.
Post Maabarot
40230, Israel
www.novipet.net
Carton right side panel
NoviPet
Joint Support
Glucosamine and Chondrotin
Warnings:
For animal use only.
Keep out of the reach of
children and animals
In case of accidental
overdose, contact a health
professional immediately.
Do not use if product
appears to be tampered
with of the foil seal is
broken. Store product in a cool, dry place.
Avoid temperatures above 86^0F.
To ensure maximum satisfaction,
this product should be kept chilled or frozen.

BACK PANEL

Cautions: Safe use in pregnant animals or animals intended for
breeding has not been proven.
Consult with veterinarian before using this product in animals; with
clotting disorders (or being treated with anticoagulant medications); with
diabetes, or any metabolic disorder causing hyperglycemia; with
a history of urinary tract stones; with known allergies to shellfish.
If lameness worsens, discontinue use and contact your veterinarian.
Administer during or after the animal has eaten to reduce incidence
of gastrointestinal upset.
Federal law prohibits the off-label use of this product in ruminants.
For use in Dogs only
Provides an excellent source of glucosamine and chondroitin
sulfate, promoting joint health and function,
Glucosamine and Chondroitin is administered as a chewable
article, providing an enjoyable, easy-to-use tasty soft chew.

DOSAGE AND ADMINISTRATION

Directions for use:
Initial Administration (4 to 6 weeks)
Under 30 lb.....................1 soft chew daily
30 -59 lb.......................2 soft chews daily
60 -99 lb.......................4 soft chews daily
100 lb and over ............... 6 soft chews daily
Maintenance:
Under 30 lb................... 1/2 soft chew daily
30 -59 lb ......................1 soft chew daily
60 -99 lb.......................2 soft Chews daily
100 lb and over................ 3 soft chews daily

PACKAGE LABEL

Novipet carton